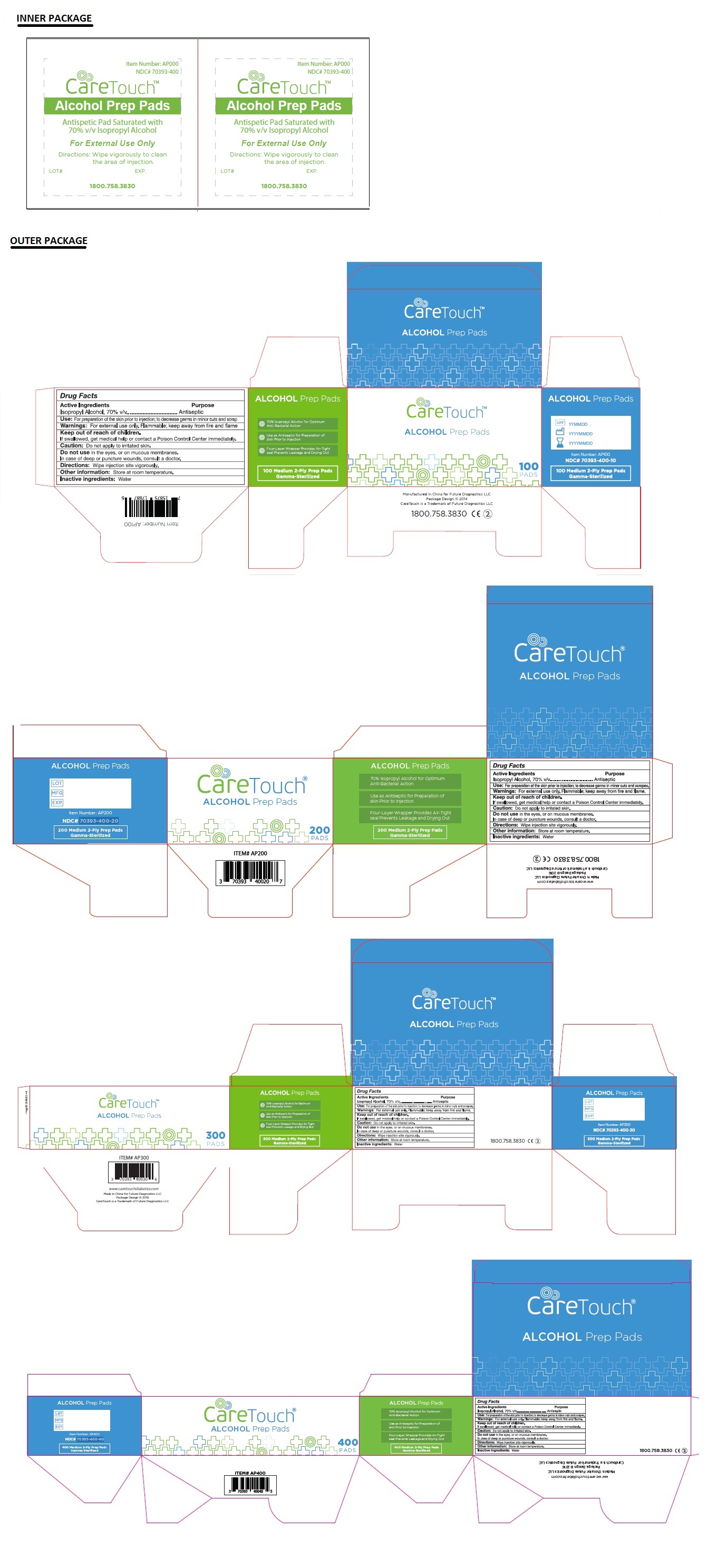 DRUG LABEL: CareTouch Alcohol Prep Pad
NDC: 70393-400 | Form: SWAB
Manufacturer: Future Diagnostics Llc
Category: otc | Type: HUMAN OTC DRUG LABEL
Date: 20251023

ACTIVE INGREDIENTS: ISOPROPYL ALCOHOL 0.7 mL/1 1
INACTIVE INGREDIENTS: WATER

CareTouch Alcohol Prep Pad

Active Ingredient

Isopropyl Alcohol, 70% V/V

Purpose

Antiseptic

Keep out of reach of children.

If swallowed, get medical help or contact a Poison Control Center immediately.

INDICATIONS AND USAGE

Use: For preparation of the skin prior to injection: to decrease germs in minor cuts and scrapes

Warnings: For external use only.

Flammable; keep away from the ﬁre and ﬂame.

Caution: Do not apply to irritated skin

Do not use in the eyes or on the mucous membranes

In case of deep or puncture wounds, consult a doctor.

DOSAGE AND ADMINISTRATION

Directions: Wipe injection site vigorously.

Other information: Store at room temperature

Inactive ingredient: Water

One Pad Saturated with 70% Isopropyl Alcohol

- 70% Isopropyl Alcohol for Optimum Anti-Bacterial Action
- Use as Antiseptic for Preparation of skin Prior to Injection
- Four-Layer Wrapper Provides Air-Tight seal Prevents Leakage and Drying Out

Made in China for Future Diagnostics LLC

CareTouch is a Trademark of Future Diagnostics LLC